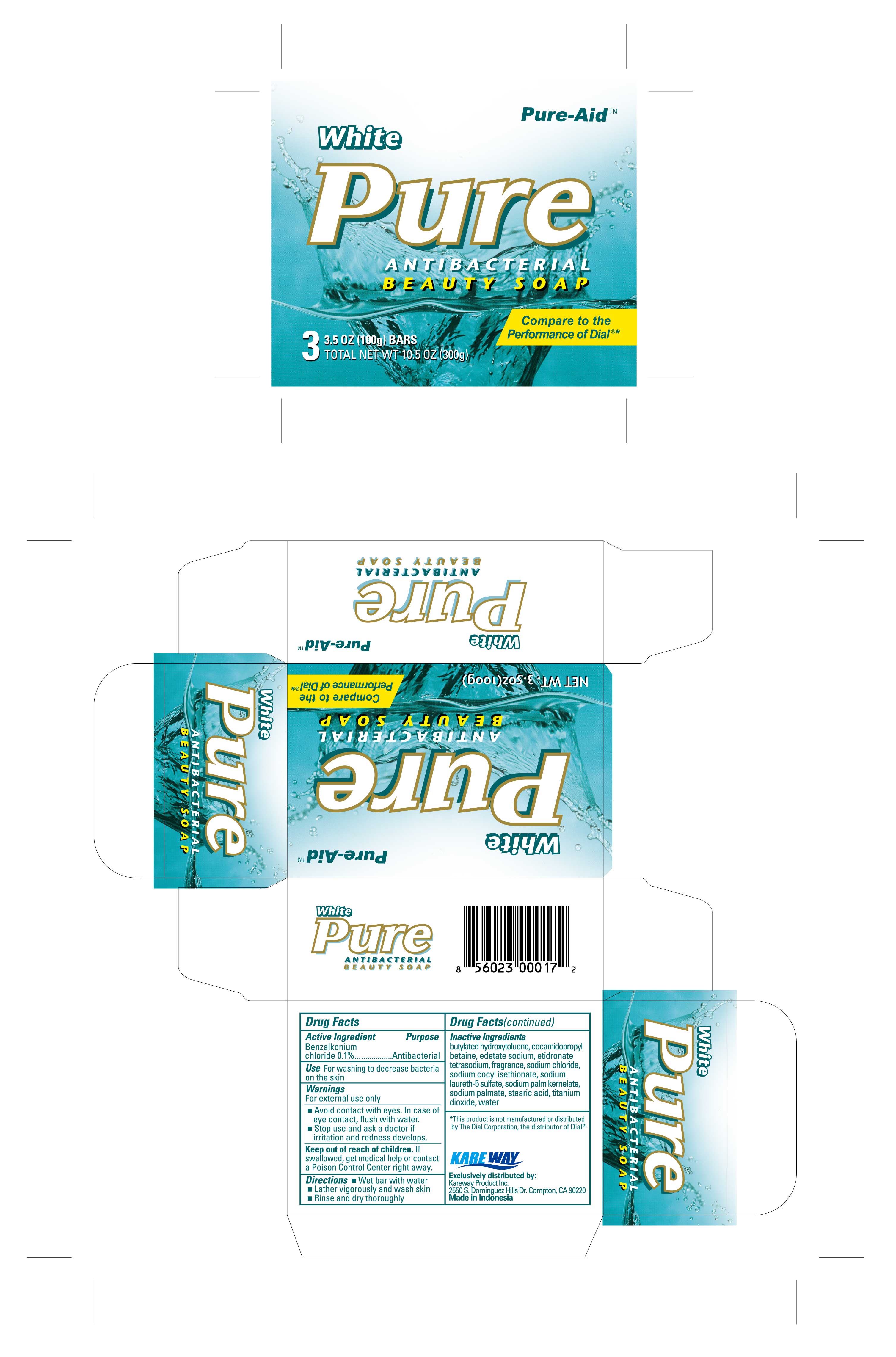 DRUG LABEL: Antibacterial Gold
NDC: 67510-0117 | Form: SOAP
Manufacturer: Kareway Product, Inc.
Category: otc | Type: HUMAN OTC DRUG LABEL
Date: 20200723

ACTIVE INGREDIENTS: BENZALKONIUM CHLORIDE 0.1 g/100 g
INACTIVE INGREDIENTS: SODIUM LAURETH-5 SULFATE; SODIUM COCOYL ISETHIONATE; EDETATE SODIUM; PEG-6 METHYL ETHER; PENTASODIUM PENTETATE; SODIUM CHLORIDE; SODIUM PALMITATE; SODIUM PALM KERNELATE; COCAMIDOPROPYL BETAINE; ETIDRONATE TETRASODIUM; WATER; BUTYLATED HYDROXYTOLUENE; TITANIUM DIOXIDE

Pure-Aid Antibacterial Beauty Soap

Active Ingredient

Benzalkonium Chloride 0.1%

Purpose

Antibacterial

Use

For washing to decrease bacteria on the skin

Warnings

For external use only

- Avoid contact with eyes. In case of eye contact, flush with water.
- Stop use and ask a doctor if irritation and redness develops.

Keep out of reach of children.

If swallowed, get medical help or contact a Poison Control Center right away.

Directions

- Wet bar with water
- Lather vigorously and wash skin
- Rinse and dry thoroghly

Inactive Ingredient

butylated hydroxytoluene, cocamidopropyl betaine, edetate sodium, etidronate tetrasodium, fragrance, sodium chloride, sodium cocyl isethionate, sodium laureth-5 sulfate, sodium palm kernelate, sodium palmate, stearic acid, titanium dioxide, water